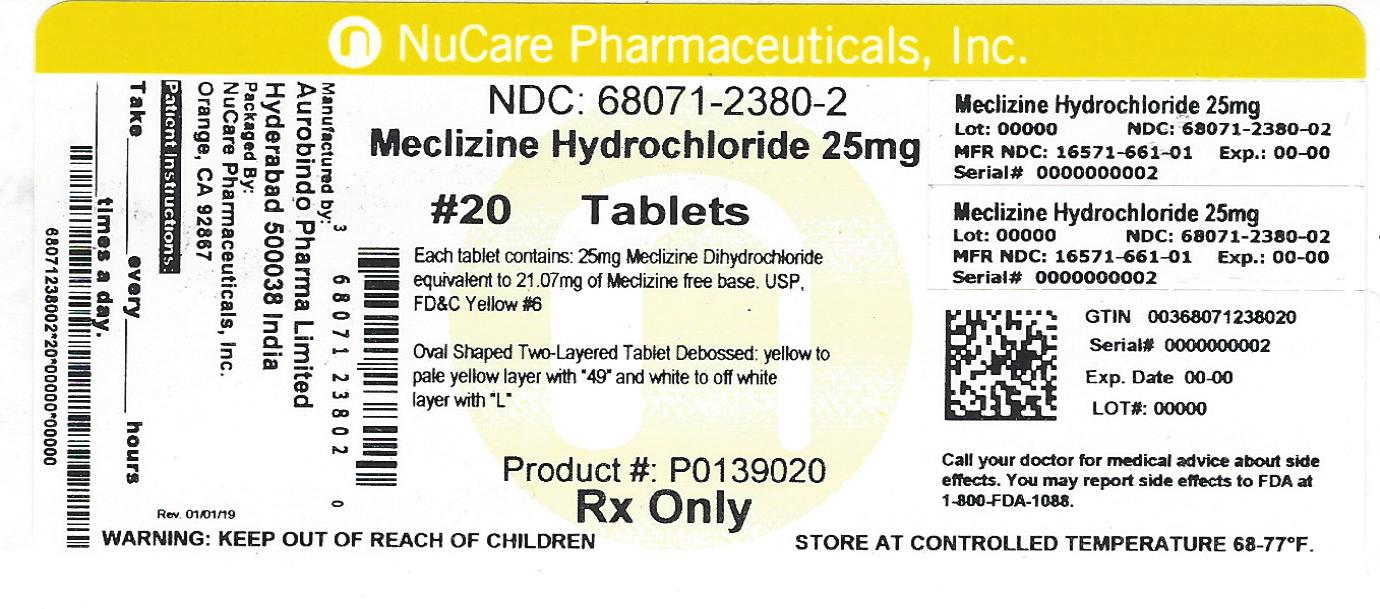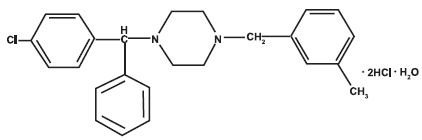 DRUG LABEL: Meclizine Hydrochloride
NDC: 68071-2380 | Form: TABLET
Manufacturer: NuCare Pharmaceuticals,Inc.
Category: prescription | Type: HUMAN PRESCRIPTION DRUG LABEL
Date: 20260302

ACTIVE INGREDIENTS: MECLIZINE HYDROCHLORIDE 25 mg/1 1
INACTIVE INGREDIENTS: STARCH, CORN; SUCROSE; WATER; POLYETHYLENE GLYCOL, UNSPECIFIED; MAGNESIUM STEARATE; ANHYDROUS DIBASIC CALCIUM PHOSPHATE; FD&C YELLOW NO. 6; D&C YELLOW NO. 10

HIGHLIGHTS OF PRESCRIBING INFORMATION

These highlights do not include all the information needed to use MECLIZINE HYDROCHLORIDE safely and effectively. See full prescribing information for MECLIZINE HYDROCHLORIDE.
MECLIZINE hydrochloride tablets, for oral use
MECLIZINE hydrochloride chewable tablets, for oral use
Initial U.S. Approval: 1957

1 INDICATIONS AND USAGE

Meclizine hydrochloride is indicated for the treatment of vertigo associated with diseases affecting the vestibular system in adults.

2 DOSAGE AND ADMINISTRATION

- Recommended dosage: 25 mg to 100 mg daily, in divided doses (2.1).
- Tablets: Swallow whole (2.2).
- Chewable Tablets: Must be chewed or crushed before swallowing; do not swallow whole (2.2).

3 DOSAGE FORMS AND STRENGTHS

- Tablets: 12.5 mg, 25 mg, and 50 mg (3).
- Chewable Tablets: 25 mg (3).

4 CONTRAINDICATIONS

Meclizine hydrochloride is contraindicated in patients with hypersensitivity to meclizine or any of the inactive ingredients.

5 WARNINGS AND PRECAUTIONS

- May cause drowsiness: Use caution when driving a car or operating dangerous machinery (5.1).
- Potential anticholinergic action: this drug should be prescribed with care to patients with a history of asthma, glaucoma, or enlargement of the prostate gland (5.2).

6 ADVERSE REACTIONS

Common adverse reactions are anaphylactic reaction, drowsiness, dry mouth, headache, fatigue, and vomiting. On rare occasions blurred vision has been reported (6).
To report SUSPECTED ADVERSE REACTIONS, contact Rising Pharmaceuticals, Inc. at 1-866-562-4597 or FDA at 1-800-FDA-1088 or www.fda.gov/medwatch.

7 DRUG INTERACTIONS

- Coadministration of meclizine hydrochloride with other CNS depressants, including alcohol, may result in increased CNS depression (7.1).
- CYP2D6 inhibitors: As meclizine is metabolized by CYP2D6, there is a potential for drug-drug interactions between meclizine hydrochloride and CYP2D6 inhibitors (7.2).

FULL PRESCRIBING INFORMATION

1 INDICATIONS AND USAGE

Meclizine hydrochloride is indicated for the treatment of vertigo associated with diseases affecting the vestibular system in adults.

2 DOSAGE AND ADMINISTRATION

2.1 Recommended Dosage

The recommended dosage is 25 mg to 100 mg daily administered orally, in divided doses, depending upon clinical response.

2.2 Administration Instructions

Tablets
Meclizine hydrochloride tablets must be swallowed whole.
Chewable Tablets
Meclizine hydrochloride chewable tablets must be chewed or crushed completely before swallowing. Do not swallow chewable tablets whole.

3 DOSAGE FORMS AND STRENGTHS

Tablets

- 12.5 mg: oval-shaped, biconvex, two-layered tablet, one blue to pale blue layer debossed with “34” and one white to off white layer debossed with “L”.
- 25 mg: oval-shaped, biconvex, two-layered tablet, one yellow to pale yellow layer debossed with “49” and one white to off white layer debossed with “L”.
- 50 mg: oval-shaped, biconvex, two-layered tablet, one blue to pale blue layer debossed with “50” and one yellow to pale yellow layer and debossed with “L”.

Chewable Tablets

- 25 mg: pink colored round tablets debossed with “M 25” on one side and break line on other side.

4 CONTRAINDICATIONS

Meclizine hydrochloride is contraindicated in patients with a hypersensitivity to meclizine or any of the inactive ingredients [see Adverse Reactions (6) and Description (11)] .

5 WARNINGS AND PRECAUTIONS

5.1 Drowsiness

Since drowsiness may occur with use of meclizine hydrochloride, patients should be warned of this possibility and cautioned against driving a car or operating dangerous machinery.
Patients should avoid alcoholic beverages while taking meclizine hydrochloride [see Drug Interactions (7.1)] .

5.2 Concurrent Medical Conditions

Because of its potential anticholinergic action, meclizine hydrochloride should be used with caution in patients with asthma, glaucoma, or enlargement of the prostate gland.

6 ADVERSE REACTIONS

The following adverse reactions associated with the use of meclizine hydrochloride were identified in clinical studies or postmarketing reports. Because some of these reactions were reported voluntarily from a population of uncertain size, it is not always possible to reliably estimate their frequency or establish a causal relationship to drug exposure.

Anaphylactic reaction, drowsiness, dry mouth, headache, fatigue, and vomiting. On rare occasions blurred vision has been reported.

7 DRUG INTERACTIONS

7.1 CNS Depressants

There may be increased CNS depression when meclizine hydrochloride is administered concurrently with other CNS depressants, including alcohol [see Warnings and Precautions (5.1)] .

7.2 CYP2D6 Inhibitors

Based on in-vitro evaluation, meclizine is metabolized by CYP2D6. Therefore, there is a possibility for a drug interaction between meclizine hydrochloride and CYP2D6 inhibitors. Therefore, monitor for adverse reactions and clinical effect accordingly.

8 USE IN SPECIFIC POPULATIONS

8.1 Pregnancy

Risk Summary
Data from epidemiological studies have not generally indicated a drug-associated risk of major birth defects with meclizine during pregnancy. However, in a published study, an increased incidence of fetal malformations was observed following oral administration of meclizine to pregnant rats during the period of organogenesis, at doses similar to those used clinically.
In the U.S. general population, the estimated background risk of major birth defects and miscarriage in clinically recognized pregnancies is 2-4% and 15-20%, respectively. The background risk of major birth defects and miscarriage for the indicated population is unknown.

Data
Human Data
Epidemiological studies reporting on pregnancies exposed to meclizine have not identified an association between the use of meclizine during pregnancy and an increased risk of major birth defects.

Animal Data
In a published study, oral administration of meclizine (25-250 mg/kg) to pregnant rats during the period of organogenesis resulted in a high incidence of fetal malformations. These effects occurred at doses as low as
25 mg/kg, which is approximately 2 times the maximum recommended human dose (100 mg) on a body surface area (mg/m2) basis.

8.2 Lactation

Risk Summary
There are no data on the presence of meclizine in human milk, the effects on the breastfed infant, or the effects on milk production. The developmental and health benefits of breastfeeding should be considered along with the mother’s clinical need for meclizine hydrochloride and any potential adverse effects on the breastfed infant from meclizine hydrochloride or from the underlying maternal condition.

8.4 Pediatric Use

Safety and effectiveness in pediatric patients have not been established.

8.5 Geriatric Use

In general, dose selection for an elderly patient should be cautious, usually starting at the low end of the dosing range, reflecting the greater frequency of decreased hepatic, renal, or cardiac function, and of concomitant disease or other drug therapy.

8.6 Hepatic Impairment

The effect of hepatic impairment on the pharmacokinetics of meclizine has not been evaluated. As meclizine hydrochloride undergoes metabolism, hepatic impairment may result in increased systemic exposure of meclizine. Treatment with meclizine hydrochloride should be administered with caution in patients with hepatic impairment.

8.7 Renal Impairment

The effect of renal impairment on the pharmacokinetics of meclizine has not been evaluated. Because of a potential for drug/metabolite accumulation, meclizine hydrochloride should be administered with caution in patients with renal impairment and in the elderly, as renal function generally declines with age.

8.8 Genetic CYP2D6 Polymorphism

The genetic polymorphism of CYP2D6 that results in poor-, intermediate-, extensive-, and ultrarapid metabolizer phenotypes could contribute to large inter-individual variability in meclizine exposure. Therefore, when meclizine hydrochloride is administered to patients with CYP2D6 polymorphism, monitor for adverse reactions and clinical effect accordingly.

11 DESCRIPTION

Meclizine hydrochloride, a histamine (H1) receptor antagonist, is a white or slightly yellowish, crystalline powder. It has the following structural formula:

Chemically, meclizine hydrochloride is 1-(p-chloro-α-phenylbenzyl)-4-(m-methylbenzyl) piperazine dihydrochloride monohydrate.
Tablets
Inactive ingredients for the tablets are: corn starch; dibasic calcium phosphate; magnesium stearate; polyethylene glycol; sucrose. The 12.5 mg tablets also contain: FD&C Blue # 1. The 25 mg tablets also contain: FD&C Yellow # 6 and D&C Yellow # 10. The 50 mg tablets also contain: FD&C Blue # 1, FD&C Yellow # 6 and D&C Yellow # 10.
Each meclizine hydrochloride 12.5 mg tablet contains 12.5 mg of meclizine dihydrochloride equivalent to 10.53 mg of meclizine free base.
Each meclizine hydrochloride 25 mg tablet contains 25 mg of meclizine dihydrochloride equivalent to 21.07 mg of meclizine free base.
Each meclizine hydrochloride 50 mg tablet contains 50 mg of meclizine dihydrochloride equivalent to 42.14 mg of meclizine free base.
Chewable Tablets
Inactive ingredients for the chewable tablets are: corn starch, colloidal silicon dioxide, FD&C Red # 40, lactose monohydrate, magnesium stearate, raspberry flavor, saccharin sodium, and talc.
Each meclizine hydrochloride 25 mg chewable tablet contains 25 mg of meclizine dihydrochloride equivalent to 21.07 mg of meclizine free base.

12 CLINICAL PHARMACOLOGY

12.1 Mechanism of Action

The precise mechanism by which meclizine exerts its therapeutic effect is unknown but is presumed to involve antagonism of the histamine H1 receptor.

12.2 Pharmacodynamics

There are no relevant pharmacodynamic data regarding meclizine.

12.3 Pharmacokinetics

The available pharmacokinetic information for meclizine following oral administration has been summarized from published literature.
Absorption
Meclizine is absorbed after oral administration with maximum plasma concentrations reaching at a median Tmax value of 3 hours post-dose (range: 1.5 to 6 hours) for the tablet dosage form.
Distribution
Drug distribution characteristics for meclizine in humans are unknown.
Elimination
Meclizine has a plasma elimination half-life of about 5-6 hours in humans.
Metabolism
In an in vitro metabolic study using human hepatic microsome and recombinant CYP enzyme, CYP2D6 was found to be the dominant enzyme for metabolism of meclizine.

13 NONCLINICAL TOXICOLOGY

13.1 Carcinogenesis, Mutagenesis, Impairment of Fertility

Carcinogenesis
Animal studies to assess the carcinogenic potential of meclizine have not been conducted.
Mutagenesis
Genetic toxicology studies of meclizine have not been conducted.
Impairment of Fertility
Animal studies to assess the effects of meclizine on fertility and early embryonic development have not been conducted.

16 HOW SUPPLIED/STORAGE AND HANDLING

16.1 How Supplied

Meclizine hydrochloride 25 mg tablets are oval shaped, biconvex, two-layered tablet, one yellow to pale yellow layer debossed with 49 and one white to off white layer debossed with L.
NDC 68071-2380-2 BOTTLES OF 20

NDC 68071-2380-3 BOTTLES OF 30

NDC 68071-2380-9 BOTTLES OF 90

16.2 Storage and Handling

Store at 20oC to 25oC (68oF to 77oF) [See USP Controlled Room Temperature].
Dispense in a tight, light-resistant container (USP).

17 PATIENT COUNSELING INFORMATION

Administration Instructions
Advise patients that the tablets must be swallowed whole, but chewable tablets must be chewed or crushed completely before swallowing [see Dosage and Administration (2.1)] .
Adverse Reactions
Advise patients that meclizine hydrochloride may cause anaphylactic reaction, drowsiness, dry mouth, headache, fatigue, vomiting and, on rare occasions, blurred vision [see Warnings and Precautions (5.1), Adverse Reactions (6)] .
Inform patients that meclizine hydrochloride may impair their ability to engage in potentially dangerous activities, such as operating machinery or vehicles.
Concomitant Drug Interactions
Advise patients regarding medications that should not be taken in combination with meclizine hydrochloride or that may necessitate increased monitoring [see Drug Interactions (7.1, 7.2)] . Inform patients that alcohol may increase adverse reactions.
Concurrent Medical Conditions
Advise patients to notify their healthcare provider about all of their medical conditions, including if they are pregnant or plan to become pregnant or if they are breastfeeding [see Warnings and Precautions (5.2), Use in Specific Populations (8.1, 8.2)] .
PIA66201-00
Distributed by:
Rising Pharmaceuticals, Inc.
Saddle Brook, NJ 07663
Issued: 08/2019